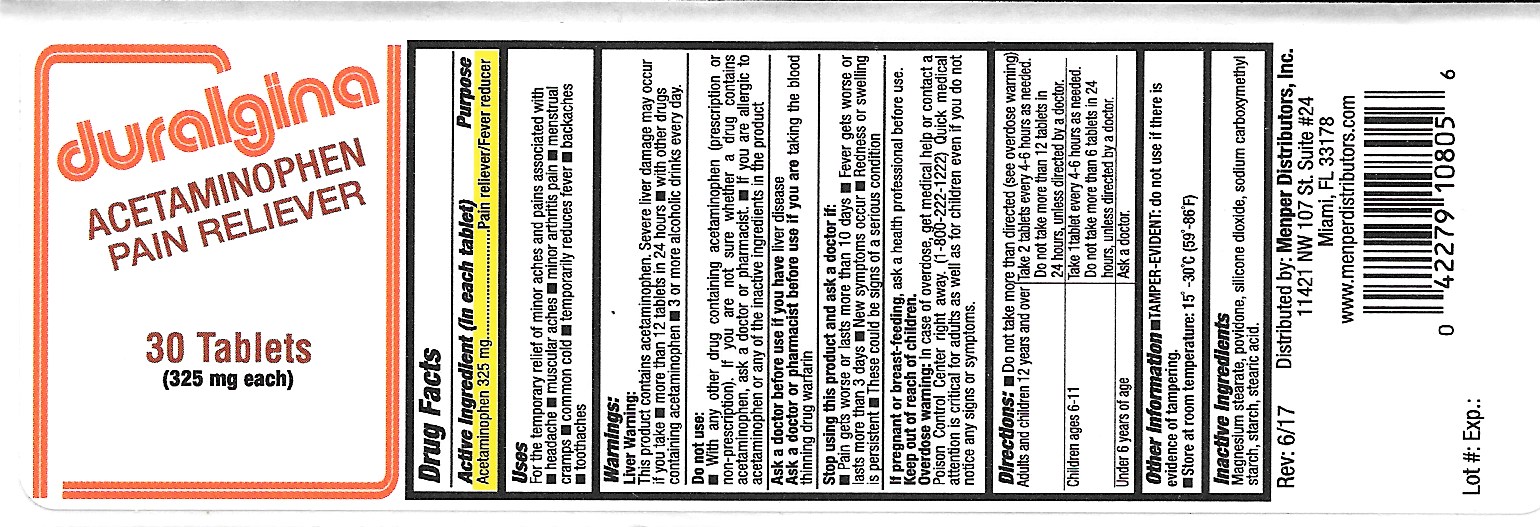 DRUG LABEL: Duralgina
NDC: 53145-013 | Form: TABLET
Manufacturer: Menper Distributors Inc.
Category: otc | Type: HUMAN OTC DRUG LABEL
Date: 20250722

ACTIVE INGREDIENTS: ACETAMINOPHEN 325 mg/1 1
INACTIVE INGREDIENTS: MAGNESIUM STEARATE; POVIDONE; SILICON DIOXIDE; CARBOXYMETHYLCELLULOSE SODIUM; STARCH, CORN; STEARIC ACID

Duralgina

Active Ingredient (in each tablet)

Acetaminophen 325 mg

Purpose

Pain reliever/Fever reducer

Uses

For the temporary relief of minor aches and pains associated with

- headache
- muscular aches
- minor arthritis pain
- menstrual cramps
- common cold
- temporarily reduces fever
- backaches
- toothaches

Warnings:

Liver warning:

This product contains acetaminophen. Sever liver damage may occur if you take

- more than12 tablets in 24 hours
- with other drugs containing acetaminophen
- 3 or more alcoholic drinks every day.

Do not use:

- with any other drug conatining acetaminophen (prescription or non-prescription). If you are not sure whether a drug contains acetaminophen, ask a doctor or pharmacist.
- If you are allergic to acetaminophen or any of the inactive ingredients in the product.

Ask a doctor before use if you have liver disease

Ask a docor or pharmacist before use if you are taking the blood thinning drug warfarin

Stop using this product and ask a doctor if:

- Pain gets worse or lasts more than 10 days
- Fever gets worse or lasts more than 3 days
- New symptoms occur
- Redness or swelling is persistent
- These could be signs of a serious condition

PREGNANCY OR BREAST FEEDING

If pregnant or breast-feeding, ask a health professional before use.

Keep out of reach of children.

Overdose warning: In case of overdose, get medical help or contact a Poison Control Center right away. (1-800-222-1222) Quick medical attention is critical for adults as well as for children even if you do not notice any signs or symptoms.

Directions:

- Do not take more than directed (see overdose warning)

Adults and children12 years and over | Take 2 tablets every 4-6 hours as needed. Do not take more than 12 tablets in 24 hours, unless directed by a doctor
Children ages 6-11 | Take 1 tablet every 4-6 hours as needed. Do not take more than 6 tablets in 24 hours, unless directed by a doctor
Under 6 years of age | Ask a doctor

INACTIVE INGREDIENT

Inactive ingredients Magnesium stearate, povidone, silicone dioxide, sodium carboxymethyl, starch, stearic acid

QUESTIONS

Questions: Call 1-800-560-5223 M-F 9AM - 4PM Eastern